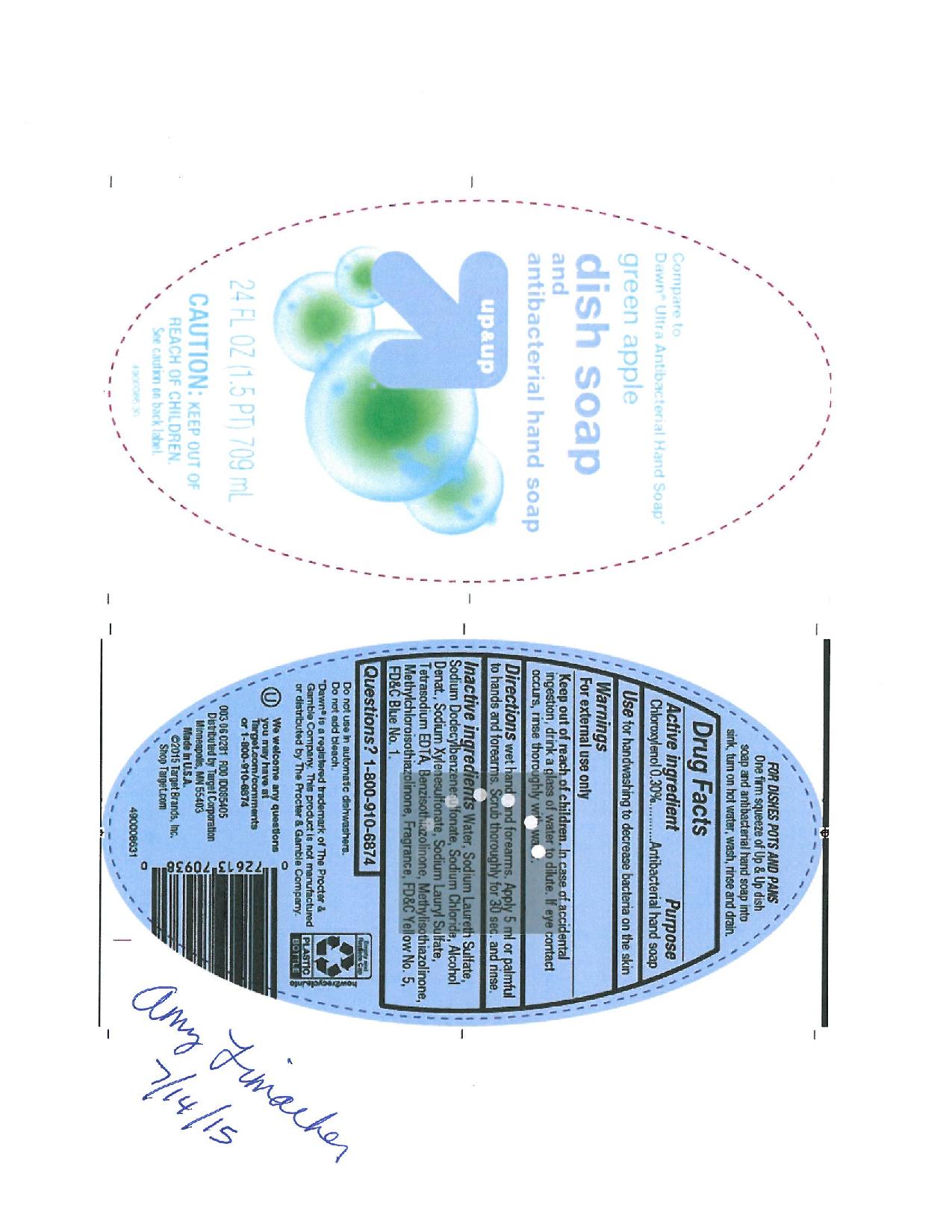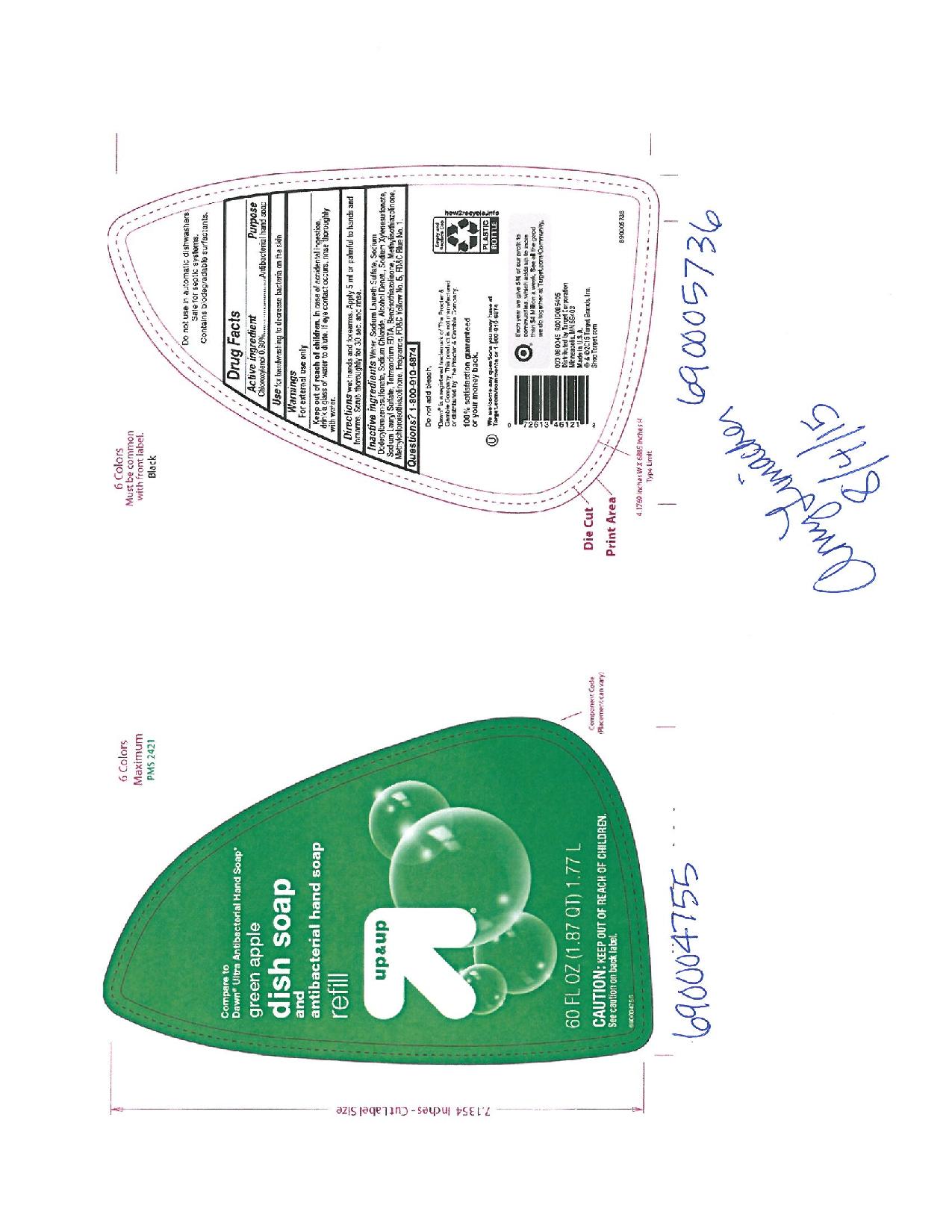 DRUG LABEL: Up (and) Up Green Apple Scent
NDC: 63691-029 | Form: SOAP
Manufacturer: Sun Products Corporation
Category: otc | Type: HUMAN OTC DRUG LABEL
Date: 20160630

ACTIVE INGREDIENTS: CHLOROXYLENOL 0.3 g/100 mL
INACTIVE INGREDIENTS: SODIUM LAURETH SULFATE; SODIUM XYLENESULFONATE; EDETATE SODIUM; BENZISOTHIAZOLINONE; WATER; SODIUM DODECYLBENZENESULFONATE; SODIUM CHLORIDE; ALCOHOL; SODIUM LAURYL SULFATE; METHYLISOTHIAZOLINONE; METHYLCHLOROISOTHIAZOLINONE; FD&C YELLOW NO. 5; FD&C BLUE NO. 1

Active Ingredient

Chloroxylenol 0.30%

Use

for handwashing to decrease bacteria on the skin

Warnings

For external use only

KEEP OUT OF REACH OF CHILDREN

In case of accidental ingestion, drink a glass of water to dilute. If eye contact occurs, rinse thoroughly with water.

DOSAGE AND ADMINISTRATION

Directions wet hands and forearms. Apply 5 ml or palmful to hands and forearms. Scrub thoroughly for 30 sec. and rinse.

Purpose

Antibacterial hand soap

Inactive ingredients

Water, Sodium Laureth Sulfate, Sodium Dodecylbenzenesulfonate, Sodium Chloride, Alcohol Denat., Sodium Xylenesulfonate, Soidum Lauryl Sulfate, Tetrasodium EDTA, Benzisothiazolinone, Methylisothiazolinone, Methylchloroisothiazolinone, Fragrance, FD&C Yello No. 5, FD&C Blue No. 1

Questions? 1-800-910-6874